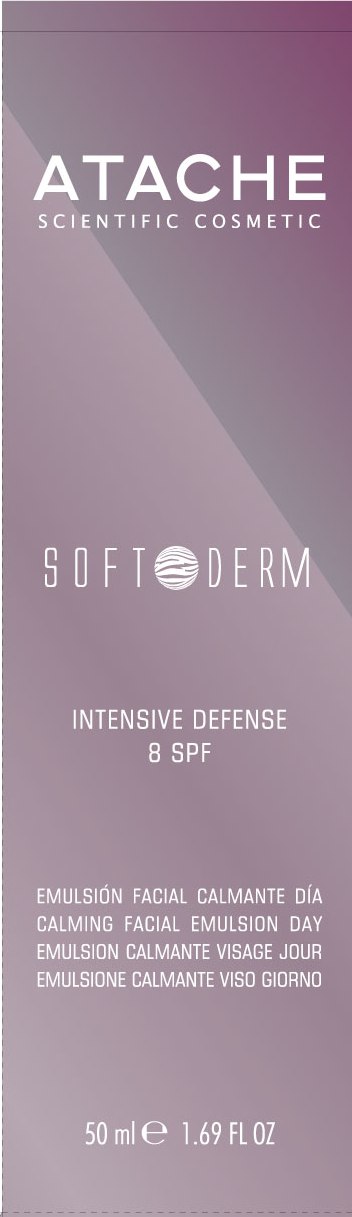 DRUG LABEL: SOFT DERM INTENSIVE DEFENSE 8 SPF
NDC: 75870-002 | Form: CREAM
Manufacturer: LABORATORIOS DE COSMETICA SCIENTIFICA  ATACHE SA
Category: otc | Type: HUMAN OTC DRUG LABEL
Date: 20110615

ACTIVE INGREDIENTS: OCTINOXATE 10 mL/50 mL; TITANIUM DIOXIDE 7.045 mL/50 mL
INACTIVE INGREDIENTS: OCTYLDODECYL MYRISTATE; PEG-6 STEARATE; GLYCERIN; ALKYL (C12-15) BENZOATE; CETYL ALCOHOL; DIMETHICONE; ALOE VERA LEAF; CAPER BERRY; CAPSOSIPHON FULVESCENS; CETETH-20; GLYCERYL MONOSTEARATE; STEARETH-20; XANTHAN GUM; ALLANTOIN; BUTYLENE GLYCOL; ALUMINUM STEARATE; HYDROXYSTEARIC ACID; ALUMINUM OXIDE; EDETATE DISODIUM; PHENOXYETHANOL; METHYLPARABEN; BUTYLPARABEN; ETHYLPARABEN; PROPYLPARABEN; ISOBUTYLPARABEN; BUTYLATED HYDROXYTOLUENE; WATER; ULVA COMPRESSA PROTEIN (ACID HYDROLYZED, 300-5000 MW)

SOFT DERM INTENSIVE DEFENSE 8 SPF

DESCRIPTION

CALMING FACIAL EMULSION DAY

Balanced facial emulsion. Specifically created for the care of sensitive skin, with effects that are relaxing, cleaning, restoring, and protective.

INSTRUCTIONS FOR USE

Directions: After cleansing and toning the skin, gently massage into the skin until fully absorbed.

WARNINGS

Warnings: For external use only. Keep out of reach of children. Avoid contact with eyes. Discontinue use if signs of irritation or rash appear.

ACTIVE INGREDIENTS:

OCTINOXATE 20% - sunscreen

TITANIUM DIOXIDE 14% - sunscreen

INACTIVE INGREDIENT

OTHER INGREDIENTS:AQUA (THERMAL WATER), ICTYLDODECYL MYRISTATE, PEG-6 STEARATE, GLYCERIN, C12-15 ALKYL BENZOATE, CETYL ALCOHOL, DIMETHICONE, ALOE BARBADENSIS GEL 10:1, CAPPARIS SPINOSA FRUIT EXTRACT, HYDROLYZED ENTEROMORPHA COMPRESSA EXTRACT, CETETH-20, GLYCERYL STEARATE, STEARETH-20, XANTUAN GUM, ALLANTOIN, BUTYLENE GLYCOL, ALUMINUM STEARATE, POLYHYDROXYSTEARIC ACID, ALUMINUM OXIDE, DISODIUM EDTA, PHENOXYETANOL, METHYLPARABEN, BUTYLPARABEN, ETHYLPARABEN, PROPYLPARABEN, ISOBUTYLPARABEN, DIMENTICONE CROSSPOLYMER, BHT, PERFUM.